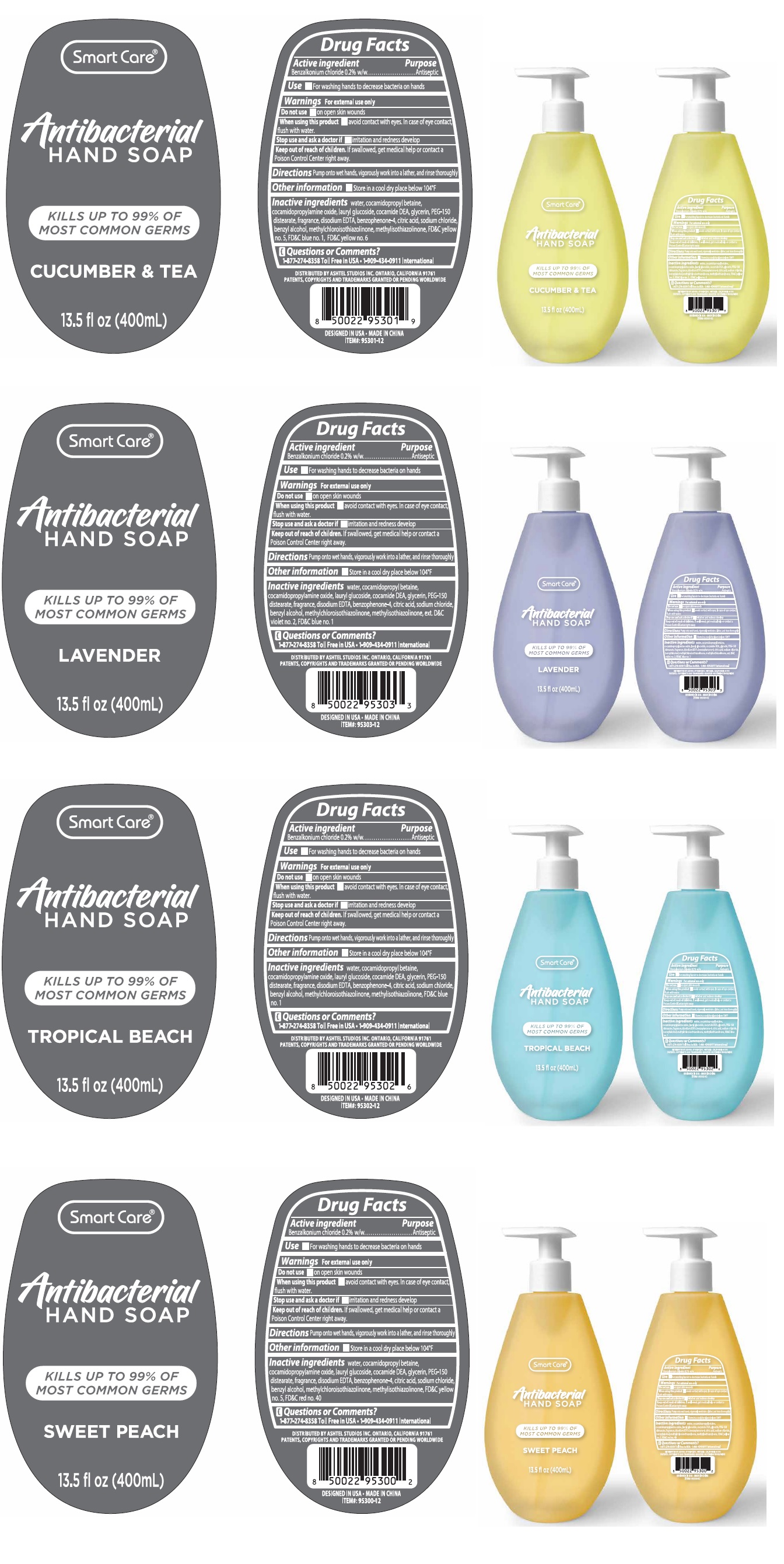 DRUG LABEL: Smart Care Antibacterial HANDSOAP
NDC: 74416-006 | Form: LIQUID
Manufacturer: Guangzhou C-kang Biotechnology Co., Ltd.
Category: otc | Type: HUMAN OTC DRUG LABEL
Date: 20210126

ACTIVE INGREDIENTS: BENZALKONIUM CHLORIDE 0.1809 g/100 mL
INACTIVE INGREDIENTS: WATER; COCAMIDOPROPYL BETAINE; COCAMIDOPROPYLAMINE OXIDE; LAURYL GLUCOSIDE; COCO DIETHANOLAMIDE; GLYCERIN; PEG-150 DISTEARATE; EDETATE DISODIUM ANHYDROUS; SULISOBENZONE; CITRIC ACID MONOHYDRATE; SODIUM CHLORIDE; BENZYL ALCOHOL; METHYLCHLOROISOTHIAZOLINONE; METHYLISOTHIAZOLINONE; FD&C BLUE NO. 1; FD&C YELLOW NO. 5; FD&C YELLOW NO. 6; EXT. D&C VIOLET NO. 2; FD&C RED NO. 40

Smart Care® Antibacterial HAND SOAP

Active ingredient

Benzalkonium chloride 0.2% w/w

Purpose

Antiseptic

Use

- For washing hands to decrease bacteria on hands

Warnings

For external use only

Do not use • on open skin wounds

When using this product • avoid contact with eyes. In case of eye contact, flush with water.

Stop use and ask a doctor if • irritation and redness develop

Keep out of reach of children. If swallowed, get medical help or contact a Poison Control Center right away.

Directions

Pump onto wet hands, vigorously work into a lather, and rinse thoroughly

Other information

- Store in a cool dry place below 104°F

Inactive ingredients

water, cocamidopropyl betaine, cocamidopropylamine oxide, lauryl glucoside, cocamide DEA, glycerin, PEG-150 distearate, fragrance, disodium EDTA, benzophenone-4, citric acid, sodium chloride, benzyl alcohol, methylchloroisothiazolinone, methylisothiazolinone, FD&C blue no. 1, FD&C yellow no. 5, FD&C yellow no. 6, ext. D&C violet no. 2, FD&C red no. 40

Questions or Comments?

1-877-274-8358 Toll Free in USA • 1-909-434-0911 International

KILLS UP TO 99% OF MOST COMMON GERMS

CUCUMBER & TEA

LAVENDER

TROPICAL BEACH

SWEET PEACH

DISTRIBUTED BY ASHTEL STUDIOS INC. ONTARIO, CALIFORNIA 91761

PATENTS, COPYRIGHTS AND TRADEMARKS GRANTED OR PENDING WORLDWIDE

DESIGNED IN USA • MADE IN CHINA